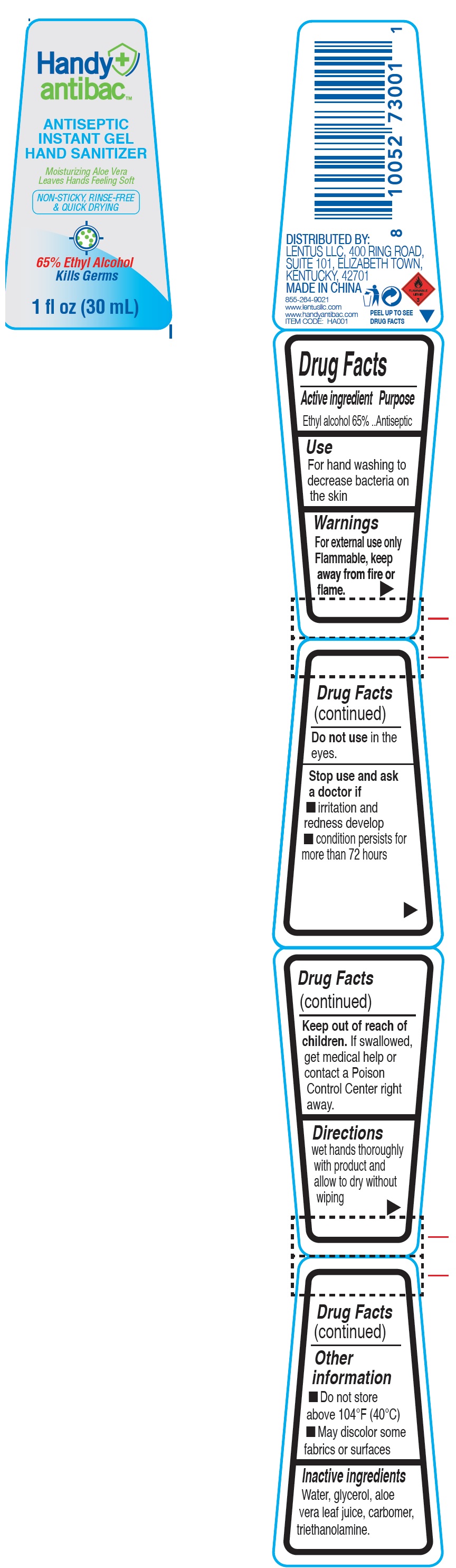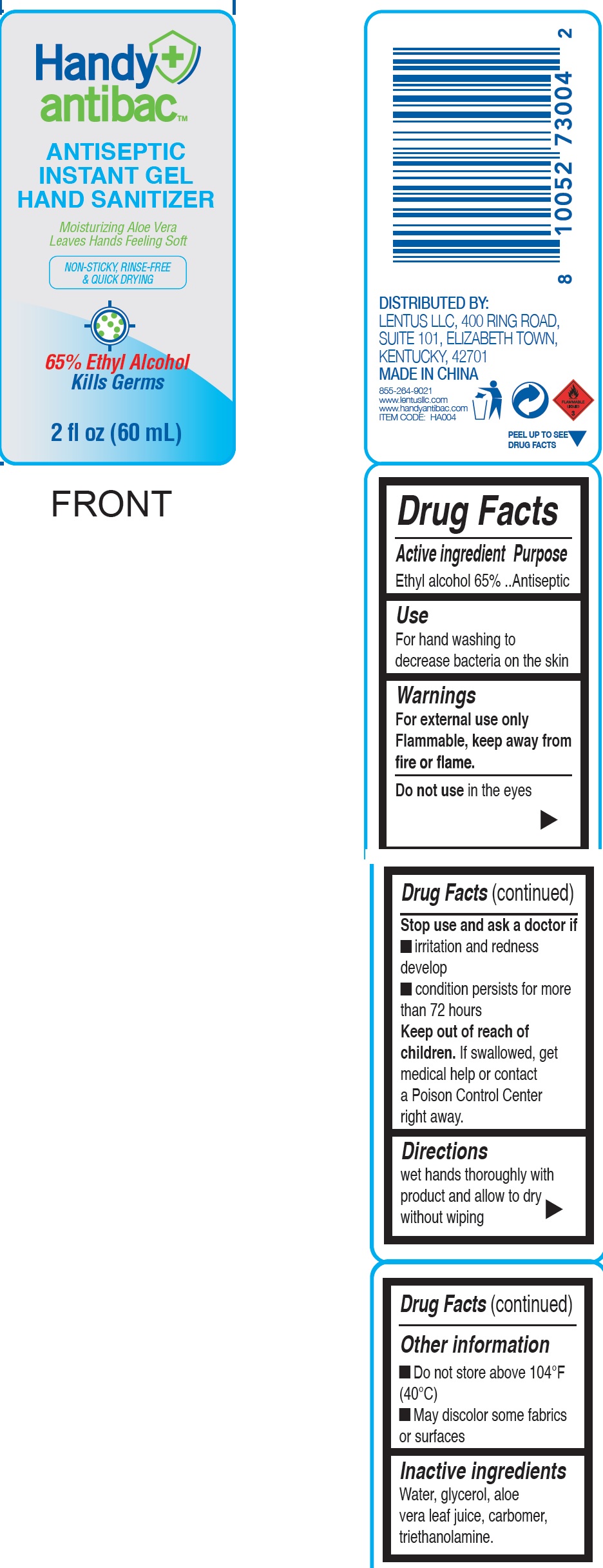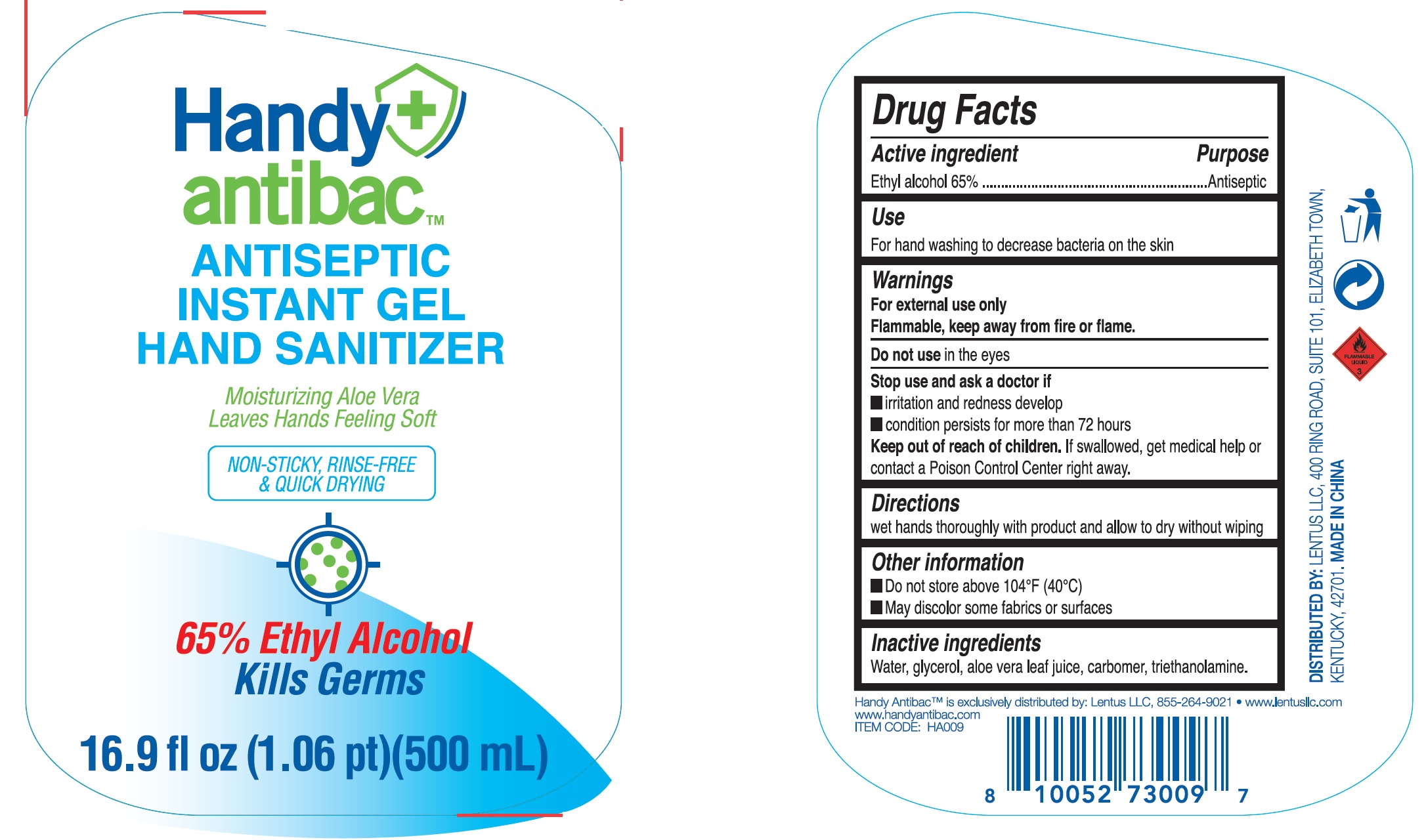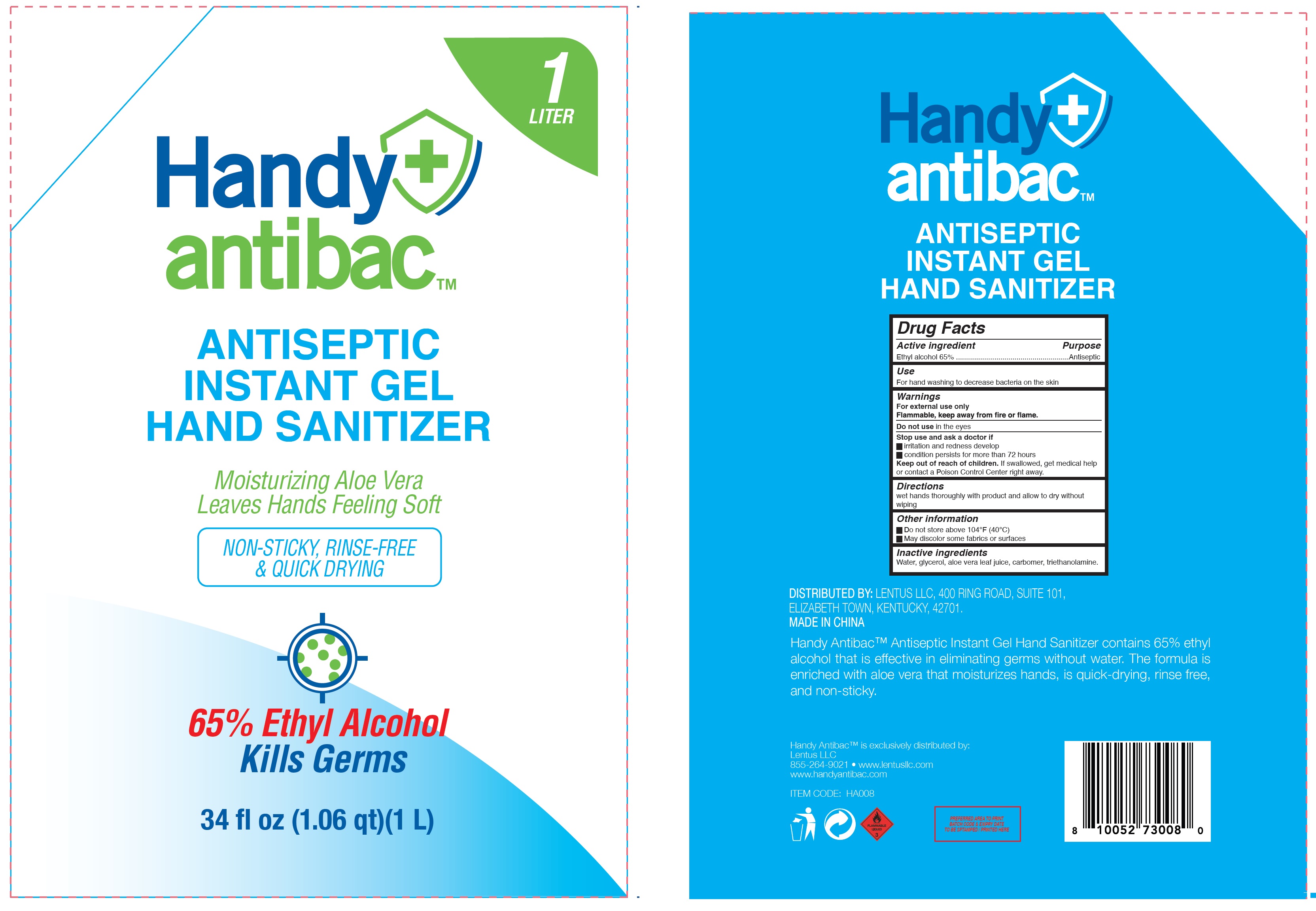 DRUG LABEL: Handy Antibac Antiseptic Instant Gel Hand Sanitizer
NDC: 79873-000 | Form: GEL
Manufacturer: Lentus LLC
Category: otc | Type: HUMAN OTC DRUG LABEL
Date: 20211008

ACTIVE INGREDIENTS: ALCOHOL 0.65 mL/1 mL
INACTIVE INGREDIENTS: WATER; GLYCERIN; ALOE VERA LEAF; CARBOMER HOMOPOLYMER, UNSPECIFIED TYPE; TROLAMINE

Handy Antibac Antiseptic Instant Gel Hand Sanitizer

Active ingredient

Ethyl alcohol 65%

Purpose

Antiseptic

Use

For hand washing to decrease bacteria on the skin

Warnings

For external use only Flammable, keep away from fire or flame.

Do not use

in the eyes.

Stop use and ask a doctor if

- irritation and redness develop
- condition persists for more than 72 hours

Keep out of reach of children.

If swallowed, get medical help or contact a Poison Control Center right away.

Directions

wet hands thoroughly with product and allow to dry without wiping

Other information

- Do not store above 104°F (40°C)
- May discolor some fabrics or surfaces

Inactive ingredients

Water, glycerol, aloe vera leaf juice, carbomer, triethanolamine.